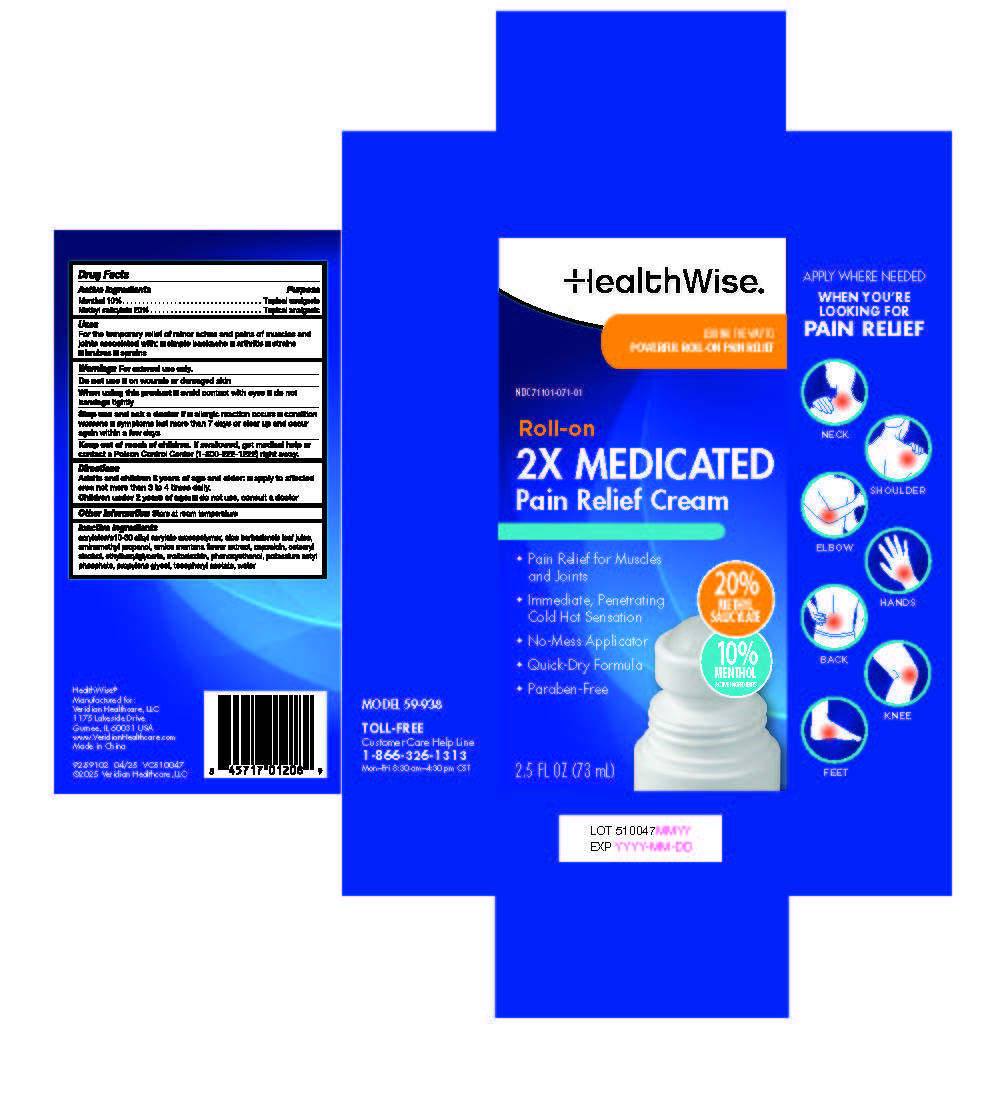 DRUG LABEL: HealthWise 2X Medicated Pain Relief Cream Roll-on
NDC: 71101-071 | Form: CREAM
Manufacturer: Veridian Healthcare
Category: otc | Type: HUMAN OTC DRUG LABEL
Date: 20250428

ACTIVE INGREDIENTS: METHYL SALICYLATE 0.2 g/1 mg; MENTHOL 0.1 g/1 mg
INACTIVE INGREDIENTS: ALOE VERA LEAF; ARNICA MONTANA FLOWER; MALTODEXTRIN; ALPHA-TOCOPHEROL ACETATE; CETEARYL ALCOHOL; AMINOMETHYLPROPANOL; PROPYLENE GLYCOL; PHENOXYETHANOL; ETHYLHEXYLGLYCERIN; WATER; CAPSAICIN; ACRYLATES/C10-30 ALKYL ACRYLATE CROSSPOLYMER (60000 MPA.S); POTASSIUM CETYL PHOSPHATE

HealthWise 2X Medicated Pain Relief Cream Roll-on

HealthWise 2X Medicated Pain Relief Cream Roll-on

Active ingredient

Menthol 10%

Methyl Salicylate 20%

Purpose

Topical analgesic

Topical analgesic

Uses

temporarily relieves minor aches and pains of muscles and joints associated with:

- arthritis
- simple backache
- strains
- sprains
- bruises

Warnings

For external use only

When using this product

- use only as directed. Read and follow all directions and warnings on this carton.
- avoid contact with eyes and mucous membranes
- rare cases of serious burns have been reported with products of this type
- do not apply to wounds or damaged, broken or irritated skin
- do not bandage tightly or apply local heat (such as heating pads) or a medicated patch to the area of use
- a transient burning sensation may occur upon application but generally disappears in several days
- if severe burning sensation occurs, discontinue use immediately
- do not expose the area treated with product to heat or direct sunlight
- avoid applying into skin folds

Stop use and ask a doctor if

- condition worsens
- redness is present
- irritation develops
- symptoms persist for more than 7 days or clear up and occur again within a few days
- you experience signs of skin injury, such as pain, swelling, or blistering where the product was applied

Flammable■ Keep away from fire or flame

If pregnant or breast-feeding,

ask a health professional before use.

Keep out of reach of children.

If swallowed, get medical help or contact a Poison Control Center (1-800-222-1222) right away.

Do not use

On wounds of damaged skin

Directions

adults and children 2 years and older:

- apply to affected area not more than 3 to 4 times daily.

children under 2 years of age: do not use, consult a doctor

Inactive ingredients

acrylates/c10-30 alkyl acrylate crosspolymer, aloe barbadensis leaf juice, aminomethyl propanol, arnica montana flower extract, capsaicin, cetearyl alcohol, ethylhexylglycerin, maltodextrin, phenoxyethanol, potassium cetyl phosphate, propylene glycol, tocopheryl acetate, water